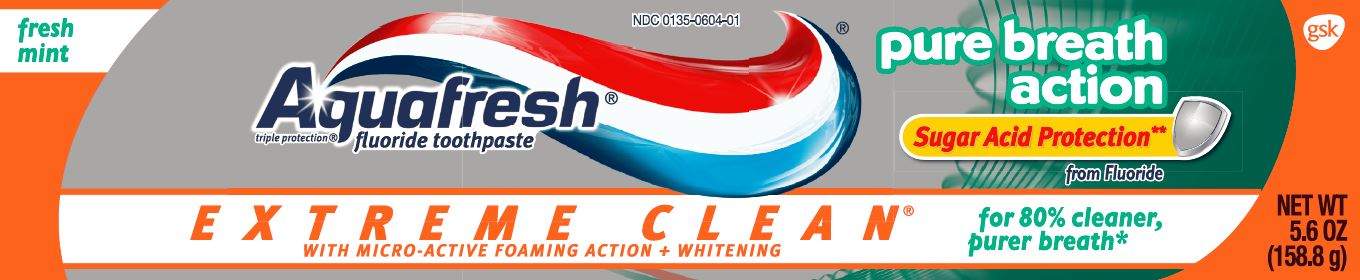 DRUG LABEL: Aquafresh

NDC: 0135-0604 | Form: PASTE
Manufacturer: Haleon US Holdings LLC
Category: otc | Type: HUMAN OTC DRUG LABEL
Date: 20240408

ACTIVE INGREDIENTS: SODIUM FLUORIDE 1.15 mg/1 g
INACTIVE INGREDIENTS: WATER; HYDRATED SILICA; SORBITOL; GLYCERIN; POLYETHYLENE GLYCOL 400; SODIUM LAURYL SULFATE; XANTHAN GUM; TITANIUM DIOXIDE; COCAMIDOPROPYL BETAINE; SODIUM CITRATE, UNSPECIFIED FORM; SACCHARIN SODIUM; ZINC CHLORIDE; FERRIC OXIDE YELLOW; D&C RED NO. 30; FD&C BLUE NO. 1

Drug Facts

Active ingredient

Sodium fluoride 0.25% (0.15% w/v fluoride ion)

Purpose

Anticavity

Use

- aids in the prevention of dental cavities.

Warnings

When using this product,

if irritation occurs discontinue use.

Keep out of reach of children under 6 years of age.

If more than used for brushing is accidentally swallowed, get medical help or contact a Poison Control Center right away.

Directions

- adults and children 2 years of age and older:
  - apply toothpaste onto a toothbrush
  - brush teeth thoroughly, preferably after each meal or at least twice a day, and not more than 3 times a day, or as directed by a dentist or doctor. Minimize swallowing. Spit out after brushing.
  - to minimize swallowing for children under 6 years of age, use a pea-sized amount and supervise brushing and rinsing until good habits are established.
- children under 2 years of age:consult a dentist or doctor.

Other information

- store below 30°C (86°F)

Inactive ingredients

water, hydrated silica, sorbitol, glycerin, PEG-8, sodium lauryl sulfate, flavor, xanthan gum, titanium dioxide, cocamidopropyl betaine, sodium citrate, sodium saccharin, zinc chloride, iron oxides, red 30, blue 1

Questions or comments?

Call toll-free 1-800-897-5623

Principal Display Panel

NDC 0135-0604-01

Aquafresh®

triple protection®

fluoride toothpaste

pure breath action

Sugar Acid Protection**

from Fluoride

EXTREME CLEAN®

WITH MICRO-ACTIVE FOAMING ACTION + WHITENING

for 80% cleaner, purer breath*

NET WT 5.6 OZ (158.8g)

fresh mint

Aquafresh®Extreme Clean®Pure Breath Action toothpaste creates micro-active foam which seeks out hard to reach places and rinses clear to leave your teeth clean and smooth. It neutralizes bad breath odors for 80% cleaner, purer breath.* Take the Feeling of Clean to the Extreme!®

**With Sugar Acid Protection provided by fluoride, which strengthens enamel, creating a shield that protects the tooth surface against sugar acid attack.

triple protection®

- healthy gums†
- strong teeth
- fresh breath

†with twice daily brushing

*immediately after brushing versus a zinc free toothpaste

ALWAYS FOLLOW THE LABEL

Trademarks are owned by or licensed to the GSK group of companies.

©2015 GSK group of companies or its licensor. All rights reserved.

GSKConsumer Healthcare

Warren, NJ 07059

1-800-897-5623

105483XA